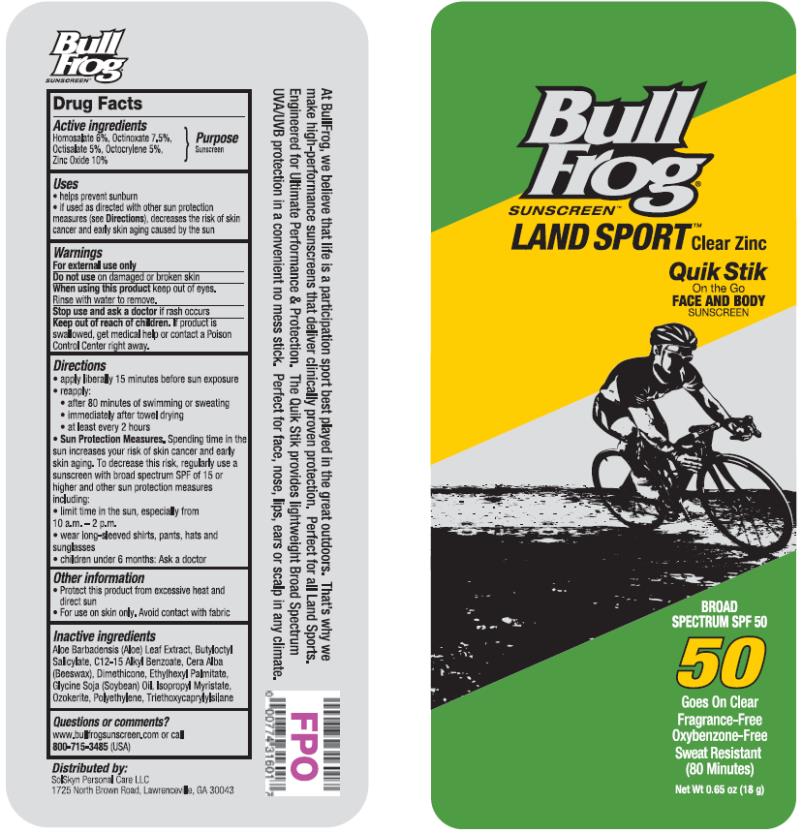 DRUG LABEL: BullFrog Land Sport SPF 50 Quik
NDC: 70281-337 | Form: STICK
Manufacturer: SolSkyn Personal Care LLC
Category: otc | Type: HUMAN OTC DRUG LABEL
Date: 20170816

ACTIVE INGREDIENTS: HOMOSALATE 6 mg/100 mg; OCTINOXATE 7.5 mg/100 mg; OCTISALATE 5 mg/100 mg; OCTOCRYLENE 5 mg/100 mg; ZINC OXIDE 10 mg/100 mg
INACTIVE INGREDIENTS: ALOE VERA LEAF; BUTYLOCTYL SALICYLATE; ALKYL (C12-15) BENZOATE; WHITE WAX; DIMETHICONE; ETHYLHEXYL PALMITATE; SOYBEAN OIL; ISOPROPYL MYRISTATE; CERESIN; HIGH DENSITY POLYETHYLENE; TRIETHOXYCAPRYLYLSILANE

BullFrog Land Sport Quik Stick SPF50

BullFrog Land Sport SPF 50 Quik Stik

Active Ingredients

Homosalate 6%, Octinoxate 7.5%, Octisalate 5%, Octocrylene 5%, Zinc Oxide 10%

Purpose

Sunscreen

Uses

• helps prevent sunburn

• if used as directed with other sun protection measures (see Directions), decreases the risk of skin cancer and early skin aging caused by the sun

Warnings

• For external use only

• Do not use

on damaged or broken skin.

• When using this product

keep out of eyes. Rinse with water to remove.

• Keep out of reach of children.

If product is swallowed, get medical help or contact a Poison Control Center right away.

Directions

• apply liberally 15 minutes before sun exposure

• re-apply:

• after 80 minutes of swimming or sweating

• immediately after towel drying

• at least every 2 hours

Sun Protection Measures. Spending time in the sun increases your risk of skin cancer and early skin aging. To decrease this risk, regularly use a sunscreen with broad spectrum SPF of 15 or higher and other sun protection measures including:

• limit time in the sun, especially from 10 a.m.-2 p.m.

• wear long-sleeved shirts, pants, hats and sunglasses

• children under 6 months: ask a doctor

Other information

• protect this product from excessive heat and direct sun

• for use on skin only. Avoid contact with fabric

Inactive Ingredients

Aloe Barbadensis (Aloe) Leaf Extract, Butyloctyl Salicylate, C12-15 Alkyl Benzoate, Cera Alba (Beeswax), Dimethicone, Ethylhexyl Palmitate, Glycine Soja (Soybean) Oil, Isopropyl Myristate, Ozokerite, Polyethylene, Triethoxycaprylylsilane

Questions or comments?

www.bullfrogsunscreen.com or call 1-800-715-3485 (USA)

PRINCIPAL DISPLAY PANEL

Bull Frog
Sunscreen
Land sport Clear Zinc
Quik Stik
On the Go
Face and Body
SPF 50